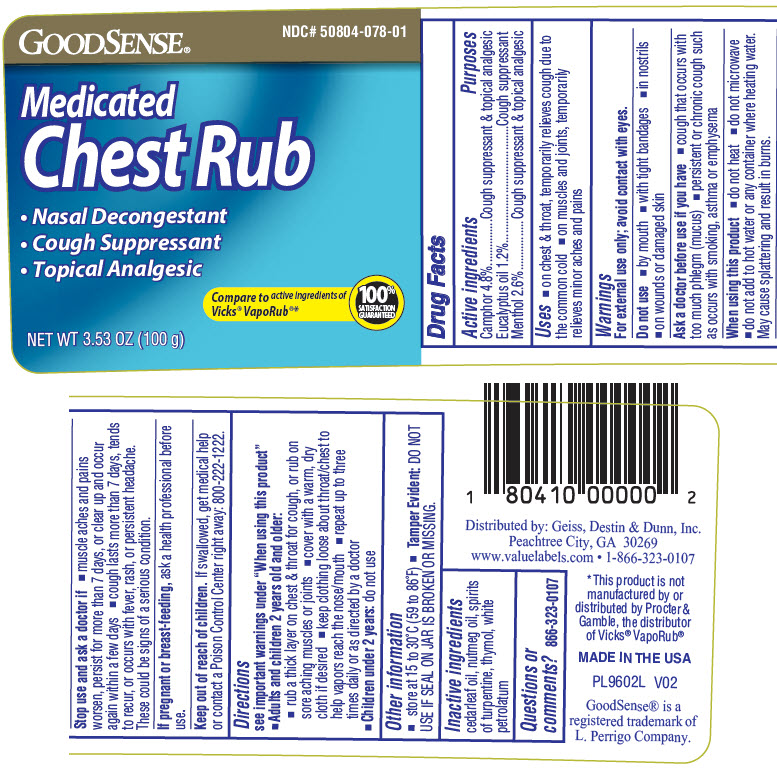 DRUG LABEL: MEDICATED CHEST RUB
NDC: 50804-078 | Form: OINTMENT
Manufacturer: GOODSENSE
Category: otc | Type: HUMAN OTC DRUG LABEL
Date: 20241231

ACTIVE INGREDIENTS: CAMPHOR (SYNTHETIC) 0.048 g/1 g; EUCALYPTUS OIL 0.012 g/1 g; MENTHOL, UNSPECIFIED FORM 0.026 g/1 g
INACTIVE INGREDIENTS: CEDAR LEAF OIL; NUTMEG OIL; TURPENTINE OIL; THYMOL; WHITE PETROLATUM

MEDICATED CHEST RUB

Drug Facts

ACTIVE INGREDIENT

PURPOSE

Active ingredients | Purposes
Camphor 4.8% | Cough suppressant & topical analgesic
Eucalyptus oil 1.2% | Cough suppressant
Menthol 2.6% | Cough suppressant & topical analgesic

Uses

- on chest & throat, temporarily relieves cough due to the common cold
- on muscles and joints, temporarily relieves minor aches and pains

Warnings

For external use only; avoid contact with eyes.

Do not use

- by mouth
- with tight bandages
- in nostrils
- on wounds or damaged skin

Ask a doctor before use if you have

- cough that occurs with too much phlegm (mucus)
- persistent or chronic cough such as occurs with smoking, asthma or emphysema

When using this product

- do not heat
- do not microwave
- do not add to hot water or any container where heating water. May cause splattering and result in burns.

Stop use and ask a doctor if

- muscle aches and pains worsen, persist for more than 7 days, or clear up and occur again within a few days
- cough lasts more than 7 days, tends to recur, or occurs with fever, rash, or persistent headache. These could be signs of a serious condition.

PREGNANCY OR BREAST FEEDING

If pregnant or breast-feeding, ask a health professional before use.

Keep out of reach of children. If swallowed, get medical help or contact a Poison Control Center right away: 800-222-1222.

Directions

see important warnings under "When using this product"

- Adults and children 2 years old and older:
  - rub a thick layer on chest & throat for cough, or rub on sore aching muscles or joints
  - cover with a warm, dry cloth if desired
  - keep clothing loose about throat/chest to help vapors reach the nose/mouth
  - repeat up to three times daily or as directed by a doctor
- Children under 2 years: do not use

Other information

- store at 15 to 30°C (59 to 86°F)
- Tamper Evident: DO NOT USE IF SEAL ON JAR IS BROKEN OR MISSING.

Inactive ingredients

cedarleaf oil, nutmeg oil, spirits of turpentine, thymol, white petrolatum

Questions or comments?

866-323-0107

Distributed by: Geiss, Destin & Dunn, Inc.
Peachtree City, GA 30269

PRINCIPAL DISPLAY PANEL - 100 g Jar Label

GOODSENSE®
NDC# 50804-078-01

Medicated
Chest Rub

- Nasal Decongestant
- Cough Suppressant
- Topical Analgesic

Compare to active ingredients of
Vicks® VapoRub®*

100%
SATISFACTION
GUARANTEED

NET WT 3.53 OZ (100 g)